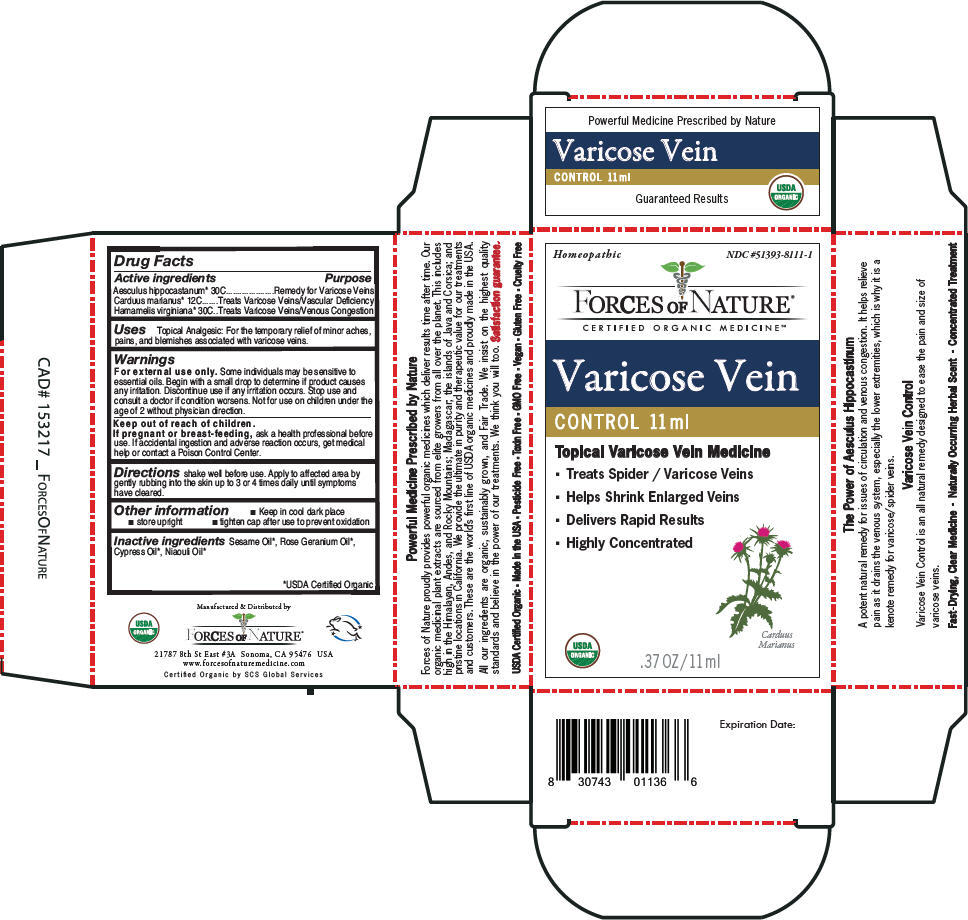 DRUG LABEL: Varicose Veins 
NDC: 51393-8111 | Form: SOLUTION/ DROPS
Manufacturer: Forces of Nature
Category: homeopathic | Type: HUMAN OTC DRUG LABEL
Date: 20210709

ACTIVE INGREDIENTS: Horse Chestnut 30 [hp_C]/100 mL; MILK THISTLE 12 [hp_C]/100 mL; Hamamelis Virginiana Root Bark/Stem Bark 30 [hp_C]/100 mL
INACTIVE INGREDIENTS: Geranium Oil, Algerian Type; Cupressus Sempervirens Leaf Oil; Niaouli Oil; Sesame Oil

FORCES OF NATURE®
Varicose Vein
CONTROL

Drug Facts

ACTIVE INGREDIENT

Active ingredients | Purpose
Aesculus hippocastanum [USDA Certified Organic] 30C | Remedy for Varicose Veins
Carduus marianus 12C | Treats Varicose Veins/Vascular Deficiency
Hamamelis virginiana 30C | Treats Varicose Veins/Venous Congestion

Uses

Topical Analgesic

For the temporary relief of minor aches, pains, and blemishes associated with varicose veins.

Warnings

For external use only. Some individuals may be sensitive to essential oils. Begin with a small drop to determine if product causes any irritation. Discontinue use if any irritation occurs. Stop use and consult a doctor if condition worsens. Not for use on children under the age of 2 without physician direction.

Keep out of reach of children.

PREGNANCY OR BREAST FEEDING

If pregnant or breast-feeding, ask a health professional before use. If accidental ingestion and adverse reaction occurs, get medical help or contact a Poison Control Center.

Directions

shake well before use. Apply to affected area by gently rubbing into the skin up to 3 or 4 times daily until symptoms have cleared.

Other information

- Keep in cool dark place
- store upright
- tighten cap after use to prevent oxidation

Inactive ingredients

Sesame Oil, Rose Geranium Oil, Cypress Oil, Niaouli Oil

Manufactured & Distributed by
FORCES OF NATURE®
21787 8th St East #3A Sonoma, CA 95476 USA

PRINCIPAL DISPLAY PANEL - 11 ml Bottle Carton

Homeopathic
NDC #51393-8111-1

FORCES OF NATURE®
CERTIFIED ORGANIC MEDICINE℠

Varicose Vein

CONTROL 11 ml

Topical Varicose Vein Medicine

- Treats Spider / Varicose Veins
- Helps Shrink Enlarged Veins
- Delivers Rapid Results
- Highly Concentrated

Carduus
Marianus

USDA
ORGANIC

.37 OZ/11 ml